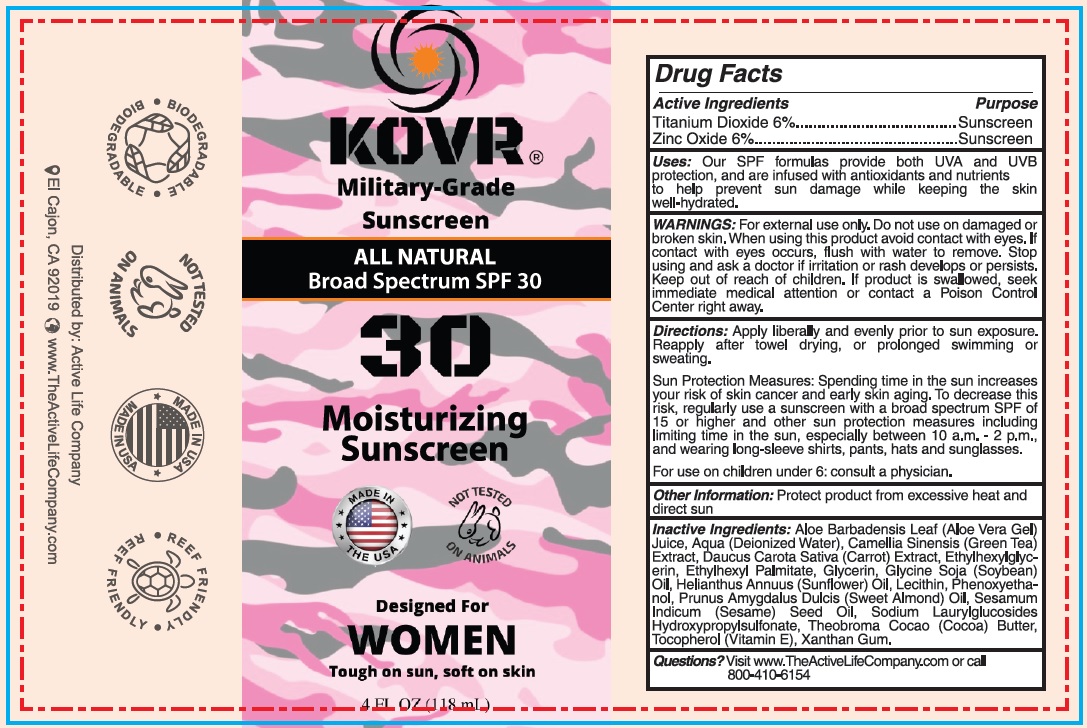 DRUG LABEL: KOVR All-Natural SPF-30 Moisturizing Sunscreen for Women
NDC: 83531-499 | Form: CREAM
Manufacturer: ACTIVE LIFE INC
Category: otc | Type: HUMAN OTC DRUG LABEL
Date: 20231111

ACTIVE INGREDIENTS: TITANIUM DIOXIDE 60 mg/1 mL; ZINC OXIDE 60 mg/1 mL
INACTIVE INGREDIENTS: ALOE VERA LEAF; WATER; GREEN TEA LEAF; CARROT; ETHYLHEXYLGLYCERIN; ETHYLHEXYL PALMITATE; GLYCERIN; SOYBEAN OIL; HELIANTHUS ANNUUS FLOWERING TOP; PHENOXYETHANOL; ALMOND OIL; SESAME OIL; SODIUM LAURYLGLUCOSIDES HYDROXYPROPYLSULFONATE; COCOA; TOCOPHEROL; XANTHAN GUM

KOVR All-Natural SPF-30 Moisturizing Sunscreen for Women

Active Ingredients

Titanium Dioxide 6% Zinc Oxide 6%

Purpose

Sunscreen

Uses:

Our SPF formulas provide both UVA and UVB protection, and are infused with antioxidants and nutrients to help prevent sun damage while keeping the skin well-hydrated.

WARNINGS:

For external use only.

Do not use

on damaged or broken skin.

When using this product

avoid contact with eyes. If contact with eyes occurs, flush with water to remove.

Stop using and ask a doctor

if irritation or rash develops or persists.

Keep out of reach of children.

If product is swallowed, seek immediate medical attention or contact a Poison Control Center right away.

Directions:

Apply liberally and evenly prior to sun exposure. Reapply after towel drying, or prolonged swimming or sweating. Spending time in the sun increases your risk of skin cancer and early skin aging. To decrease this risk, regularly use a sunscreen with a broad spectrum SPF of 15 or higher and other sun protection measures including limiting time in the sun, especially between 10 a.m. - 2 p.m., and wearing long-sleeve shirts, pants, hats and sunglasses. For use on children under 6: consult a physician.
Sun Protection Measures:

Other Information:

Protect product from excessive heat and direct sun

Inactive Ingredients:

Aloe Barbadensis Leaf (Aloe Vera Gel) Juice, Aqua (Deionized Water), Camellia Sinensis (Green Tea) Extract, Daucus Carota Sativa (Carrot) Extract, Ethylhexylglycerin, Ethylhexyl Palmitate, Glycerin, Glycine Soja (Soybean) Oil, Helianthus Annuus (Sunflower) Oil, Lecithin, Phenoxyethanol, Prunus Amygdalus Dulcis (Sweet Almond) Oil, Sesamum Indicum (Sesame) Seed Oil, Sodium Laurylglucosides Hydroxypropylsulfonate, Theobroma Cocao (Cocoa) Butter, Tocopherol (Vitamin E), Xanthan Gum.

Questions?

Visit www.TheActiveLifeCompany.com or call 800-410-6154